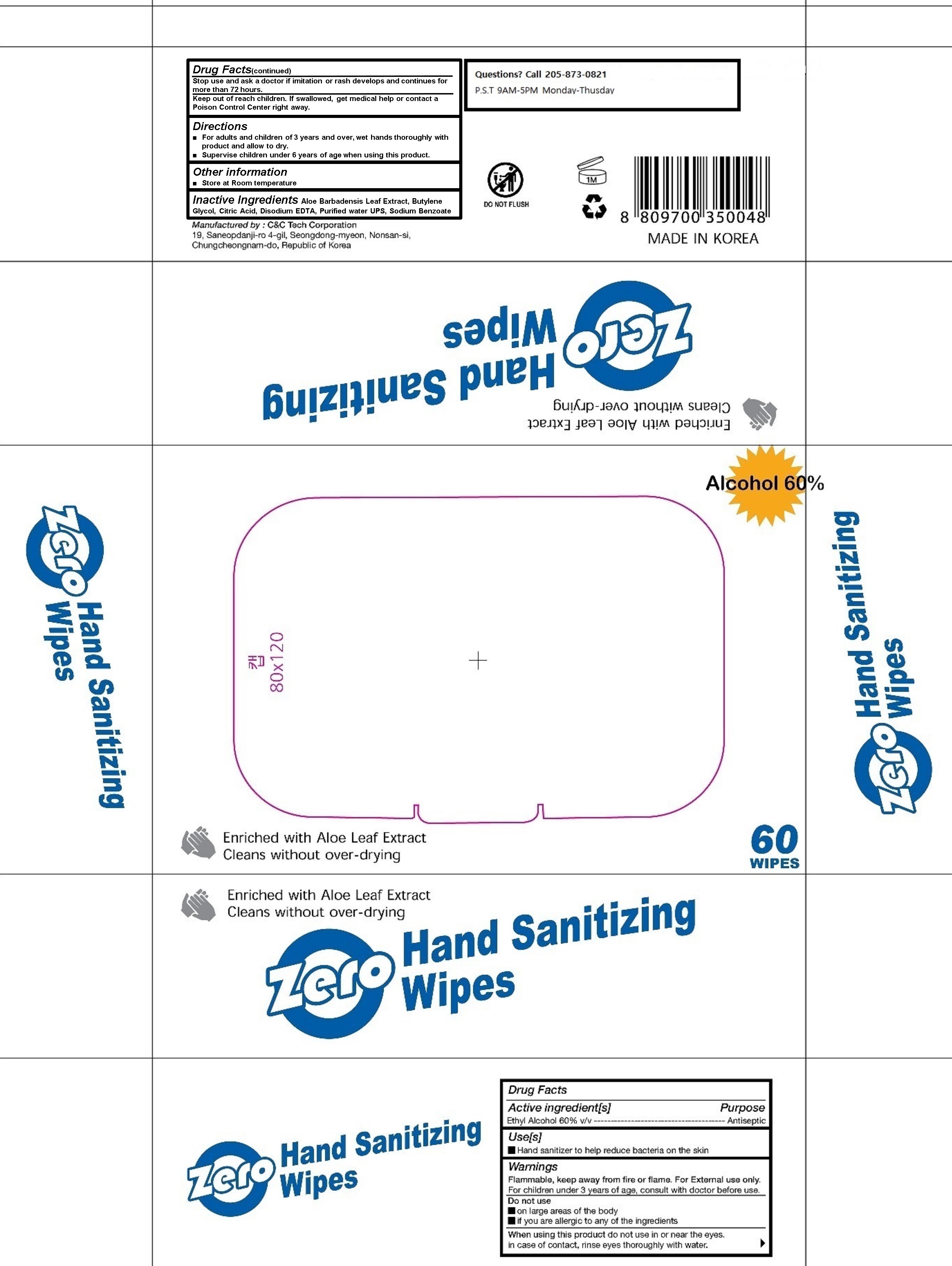 DRUG LABEL: Zero Hand Sanitizing Wipes
NDC: 80048-001 | Form: CLOTH
Manufacturer: C&C Tech Co., Ltd.
Category: otc | Type: HUMAN OTC DRUG LABEL
Date: 20200925

ACTIVE INGREDIENTS: ALCOHOL 60 g/100 g
INACTIVE INGREDIENTS: ETHYLHEXYLGLYCERIN; CITRIC ACID MONOHYDRATE; ALOE VERA LEAF; BUTYLENE GLYCOL; EDETATE DISODIUM ANHYDROUS; SODIUM BENZOATE; DIPROPYLENE GLYCOL; GLYCERYL CAPRYLATE; GLYCERIN; WATER; POLYSORBATE 20; CAPRYLYL GLYCOL

Active Ingredient(s)

Ethyl Alcohol 60% v/v. Purpose: Antiseptic

Purpose

Antiseptic

Use

Hand Sanitizer to help reduce bacteria on the skin

Warnings

Flammable, keep away from heat or flame. For external use only.

Do not use

- on large areas of the body
- if you are allegic to any of the ingredients

When using this product do not use in or near the eyes.

In case of contact, rinse eyes thoroughly with water.

Stop use and ask a doctor if irritation or rash develops and continues for more than 72 hours.

Keep out of reach of children. If swallowed, get medical help or contact a Poison Control Center right away.

Directions

- For adults and children of 3 years and over, wet hands thoroughly with product and allow to dry.
- Supervise children under 6 years of age when using this product.

Other information

- Store at room temperature

Inactive ingredients

Purified water USP, Sodium Benzoate, Citric Acid, Disodium EDTA, Aloe Barbadensis Leaf Extract, Butylene Glycol